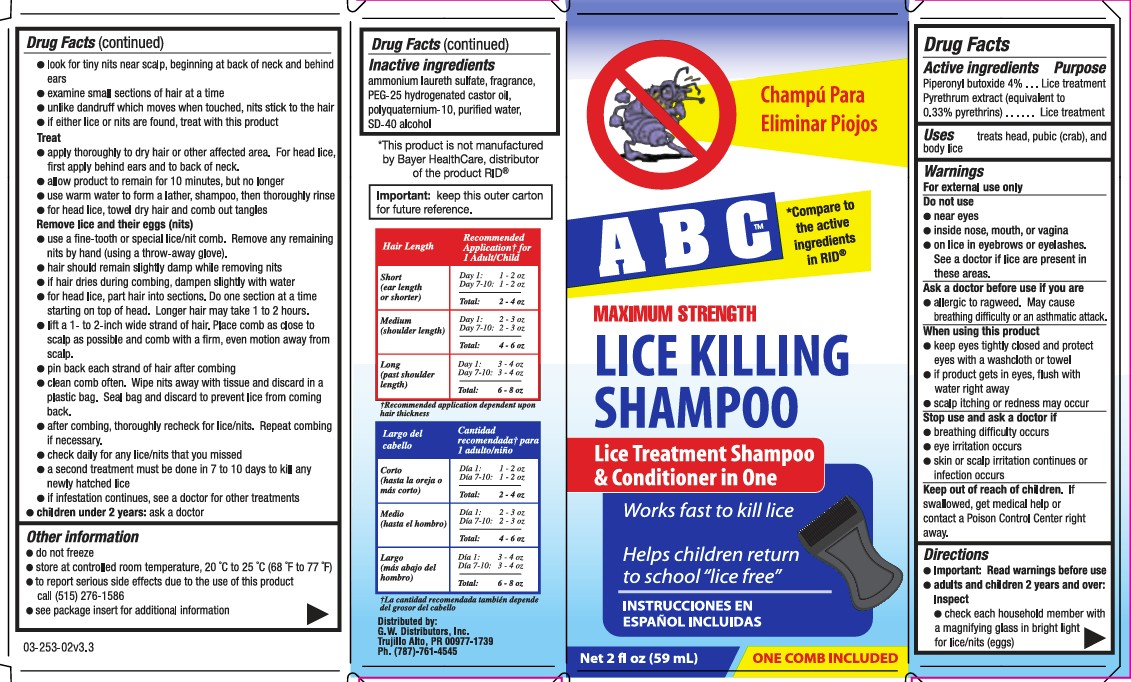 DRUG LABEL: ABC Lice Killing
NDC: 11383-312 | Form: SHAMPOO
Manufacturer: Weeks & Leo Co., Inc.
Category: otc | Type: HUMAN OTC DRUG LABEL
Date: 20251029

ACTIVE INGREDIENTS: PYRETHRUM EXTRACT 0.33 g/100 mL; PIPERONYL BUTOXIDE 4 g/100 mL
INACTIVE INGREDIENTS: ALCOHOL; WATER; POLYQUATERNIUM-10 (400 CPS AT 2%); PEG-25 HYDROGENATED CASTOR OIL; AMMONIUM LAURETH-2 SULFATE

ABC Lice Killing Shampoo

Active Ingredient

Piperonyl butoxide 4%

Pyrethrum extract (equivalent to 0.33% pyrethrins)

Purposes

Lice Treatment

Uses

treats head, pubic (crab), and body lice

Warnings

For external use only

Do not use

near eyes
inside nose, mouth, or vagina
on lice in eyebrows or eyelashes. See a doctor if lice are present in these areas.

if you have ever had an allergic reaction to this product or any of its ingredients

Ask doctor before use if you are

allergic to ragweed. May cause breathing difficulty or an asthmatic attack

When using this product

keep eyes tightly closed and protect eyes with a washcloth or towel
if product gets into eyes, flush with water right away
scalp itching or redness may occur

Stop and ask a doctor if

breathing difficulty occurs
eye irritation occurs
skin or scalp irritation continues or infection occurs

Keep out of reach of children

If swallowed, get medical help or contact a Poison Control Center (1-800-222-1222) right away.

Directions

Important: Read warnings before use
Adults and children 2 years and over

Inspect

check each household member with a magnifying glass in bright light for lice/nits (eggs)
look for tiny nits near scalp, beginning at back of neck and behind ears
examine small sections of hair at a time
unlike dandruff which moves when touched, nits stick to the hair
if either lice or nits are found, treat with this product

Treat

apply thoroughly to DRY HAIR or other affected area. For head lice, first apply behind ears and to back of neck.
allow product to remain for 10 minutes, but no longer
use warm water to form a lather, shampoo, then thoroughly rinse
for head lice, towel dry hair and comb out tangles

Remove lice and their eggs (nits)

se a fine-tooth or special lice/nit comb. Remove any remaining nits by hand (using a throw-away glove).
hair should remain slightly damp while removing nits
if hair dries during combing, dampen slightly with water
for head lice, part hair into sections. Do one section at a time starting on top of the head. Longer hair may take 1 to 2 hours.
lift a 1-to 2-inch wide strand of hair. Place comb as close to scalp as possible and comb with a firm, even motion away from scalp.
pin back each strand of hair after combing
clean comb often. Wipe nits away with tissue and discard in a plastic bag. Seal bag and discard to prevent lice from coming back.
after combing, thoroughly recheck for lice/nits. Repeat combing if necessary.
check daily for any lice/nits that you missed
a second treatment must be done in 7 to 10 days to kill any newly hatched lice
if infestation continues, see a doctor for other treatments
Children under 2 years: ask a doctor

Other Information

do not freeze
store at controlled room temperature 20°-25°C (68°-77°F)
see package insert for additional information

Inactive Ingredients

ammonium laureth sulfate, fragrance, PEG-25 hydrogenated castor oil, polyquaternium-10, purified water, SD-40 alcohol

Questions or comments?

to report serious side effects due to the use of this product call 1-877-974-7167

Additional Information

Hair Length - Recommended Application for 1 Adult/Child

Short (ear length or shorter) Day 1: 1-2 oz; Day 7-10: 1-2oz; Total : 2-4oz

Medium (shoulder length) Day1: 2-3oz; Day 7-10: 2-3oz; Total: 4-6oz

Long (past shoulder length) Day 1: 3-4oz; Day 7-10: 3-4oz; Total: 6-8oz

Important: keep this outer carton for future reference

Package Insert

Consumer Information

LICE KILLING SHAMPOO

For the treatment of Head Lice, Pubic (Crab) Lice and Body Lice

DIRECTIONS

Important: Read warnings before using this product. A second treatment must be done in 7-10 days to kill anu newly hatched lice eggs (nits)

Inspect

examine each household member with a magnifying glass in bright light for lice/eggs (nits)
look for tiny eggs (nits) near scalp, beginning at the back of neck and behind ears
examine small sections of hair
eggs (nits) stick to the hair
if either lice or eggs (nits) are found, treat with this product

Treat

apply thoroughly to dry hair or other affected area. For head lice, first apply behind ears and to back of neck
allow product to remain for 10 minutes but no longer
use warm water to form a lather, shampoo, then thoroughly rinse
for head lice, towel dry hair and comb out tangles

To Remove Lice and Their Eggs (Nits)

use a special lice/nit or fine-toothed comb (included). Remove any remaining eggs (nits) by hand, using a throwaway glove
hair should remain slightly damp while removing eggs (nits)
if hair dries during combing, dampen slightly with water
for head lice, part hair into sections. Do one section at a time starting on top of the head. Longer hair may take 1 to 2 hours
lift a 1- to 2-inch wide strand of hair. Place comb firm, even motion away from scalp
pin back each strand of hair after combing
clean comb often. Wipe eggs (nits) away with tissue and discard in a plastic bag. Seal bag and discard to prevent lice from coming back
after combing, thoroughly recheck for lice/eggs (nits). Repeat combing if necessary
check daily for any lice/eggs (nits) that you missed
a second treatment must be done within 7 to 10 days to kill any newly hatched lice/eggs (nits)
if infestation continues, see a doctor for other treatments

1. HEAD LICE

head lice lay small white eggs (nits) on the hair shaft close to the scalp
eggs (nits) are most easily found on the back of the neck or behind the ears
disinfect hats, hair ribbons, scarves, coats, towels and bed linens by machine washing in hot water [above 54 C (130 F)], then using the hottest dryer setting for at least 20 minutes
items that cannot be washed, dry cleaned or stored may be sprayed with a product designed for this purpose
soak all combs and brushes in hot water [above 54 C (130 F)] for at least 10 minutes
vacuum all carpets, mattresses, upholstered furniture, and car seats that may have been used by affected people

2. PUBIC (CRAB) LICE

pubic (crab) lice may be contracted by sexual contact
sexual partners should be treated simultaneously to avoid reinfestation
lice are very small and look like brown or grey dots on the skin
pubic (crab) lice usually cause intense itching and lay small white eggs (nits) on the hair shaft generally close to the skin surface
pubic (crab) lice may be present on the short hairs of the groin, thighs, trunk, and underarms, -and occasionally on the beard, eyelids, and mustache
disinfect underwear by machine washing in hot water [above 54 C (130 F)], then using the hottest dryer setting for at least 20 minutes

3. BODY LICE

body lice and their eggs (nits) are generally found in the seams of clothing, particularly in the waistline and armpit areas
body lice feed on skin then return to clothing to lay their eggs (nits)
disinfect clothing by machine washing in hot water [above 54 C (130 F)], then using the hottest dryer setting for at least 20 mintues
do not seal clothing in a plastic bag because eggs (nits) can remain dormant for up to 30 days

Save this insert for future reference

SHAKE WELL BEFORE USING

PACKAGE LABEL

ABC

Maximum Strength

Lice Killing Shampoo

Lice Treament Shampoo & Conditioner

Works fast to kill lice

Sends children back to school "lice free"

2 fl oz (59 mL)

Includes One Lice Comb